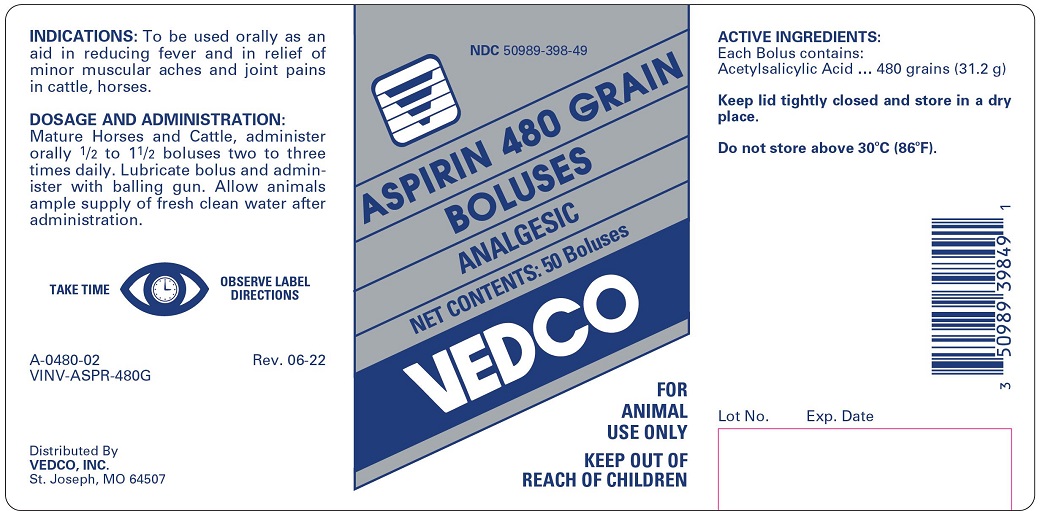 DRUG LABEL: ASPIRIN 
NDC: 50989-398 | Form: TABLET
Manufacturer: Vedco, Inc.
Category: animal | Type: OTC ANIMAL DRUG LABEL
Date: 20221013

ACTIVE INGREDIENTS: ASPIRIN 31.2 g/1 1

Aspirin 480 Grain Boluses ANALGESIC

INDICATIONS

To be used orally as an aid in reducing fever and in relief of minor muscular aches and joint pains in cattle, horses.

DOSAGE AND ADMINISTRATION

Mature Horses and Cattle, administer orally 1/2 to 1 1/2 Boluses two to three times daily. Lubricate bolus and administer with balling gun. Allow Animals ample supply of fresh clean water after administration.

TAKE TIME OBSERVE LABEL DIRECTIONS

ACTIVE INGREDIENTS

Each Bolus contains:

Acetylsalicylic Acid ... 480 grains (31.2 g)

STORAGE AND HANDLING

Keep lid tightly closed and store in a dry place

Do not store above 30o C (86o F)